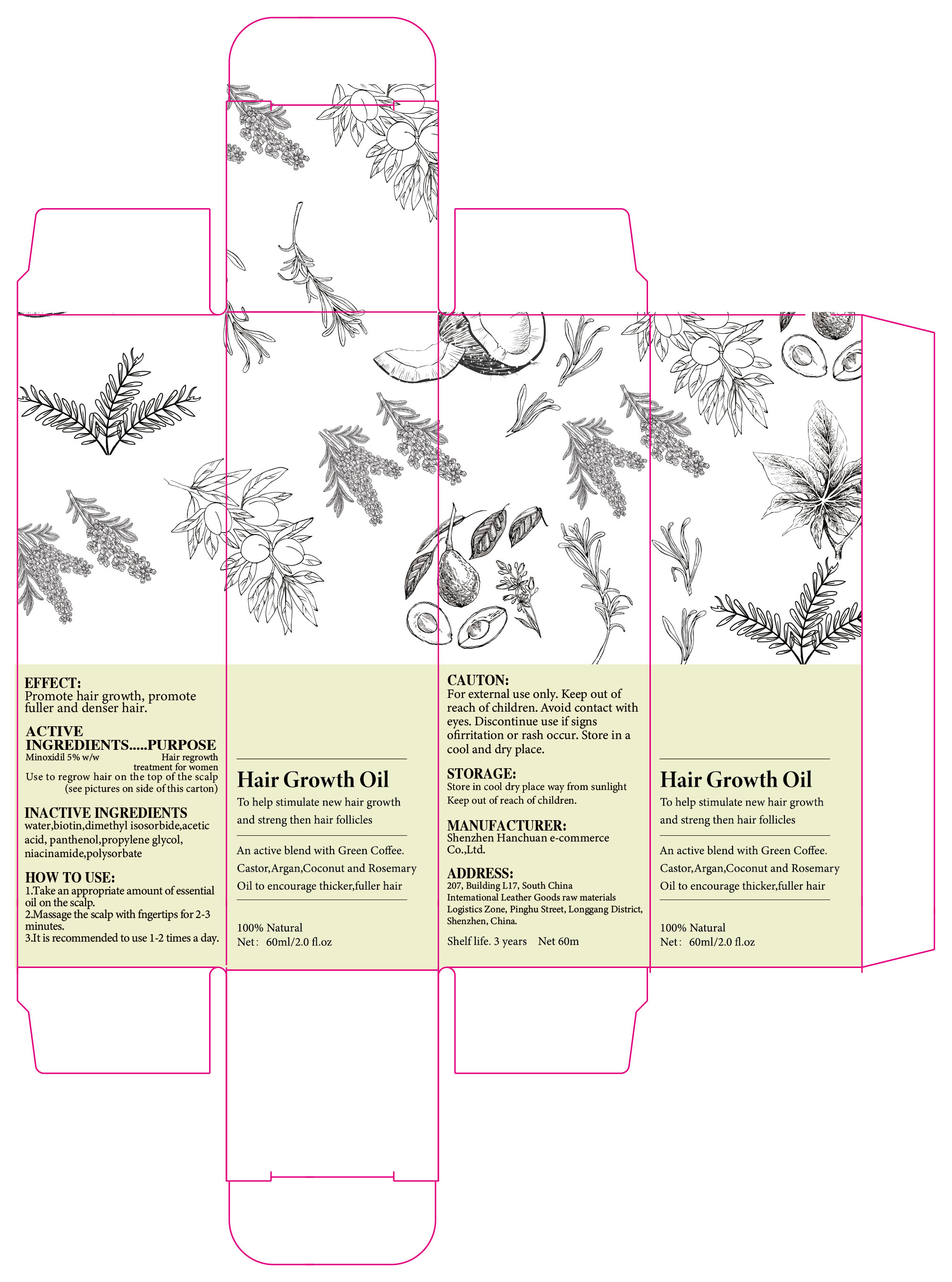 DRUG LABEL: Hair Growth Oil
NDC: 84302-003 | Form: LIQUID
Manufacturer: Shenzhen Hanchuan e-commerce Co., Ltd
Category: otc | Type: HUMAN OTC DRUG LABEL
Date: 20240515

ACTIVE INGREDIENTS: MINOXIDIL 5 g/100 mL
INACTIVE INGREDIENTS: WATER; BIOTIN; ACETIC ACID; PROPYLENE GLYCOL; POLYSORBATE 80; NIACINAMIDE; DIMETHYL ISOSORBIDE; PANTHENOL

Hair Growth Oil

ACTIVE INGREDIENT

Minoxidil 5%

PURPOSE

Hair regrowth treatment for women Use to regrow hair on the top of the scalp

Keep out of reach of children.

INDICATIONS AND USAGE

To help stimulate new hair growthand streng then hair follicles

WARNINGS

For external use only. Keep out ofreach of children. Avoid contact witheyes. Discontinue use if signsofirritation or rash occur. Store in acool and dry place.

DOSAGE AND ADMINISTRATION

1.Take an appropriate amount of essentialoil on the scalp.
2.Massage the scalp with fngertips for 2-3minutes.
3.It is recommended to use 1-2 times a day

STORAGE AND HANDLING

Keep out ofreach of children. Avoid contact witheyes. Discontinue use if signsofirritation or rash occur. Store in acool and dry place.

INACTIVE INGREDIENT

water
biotin
dimethyl isosorbide
acetic acid
panthenol
propylene glycol
niacinamide
polysorbate